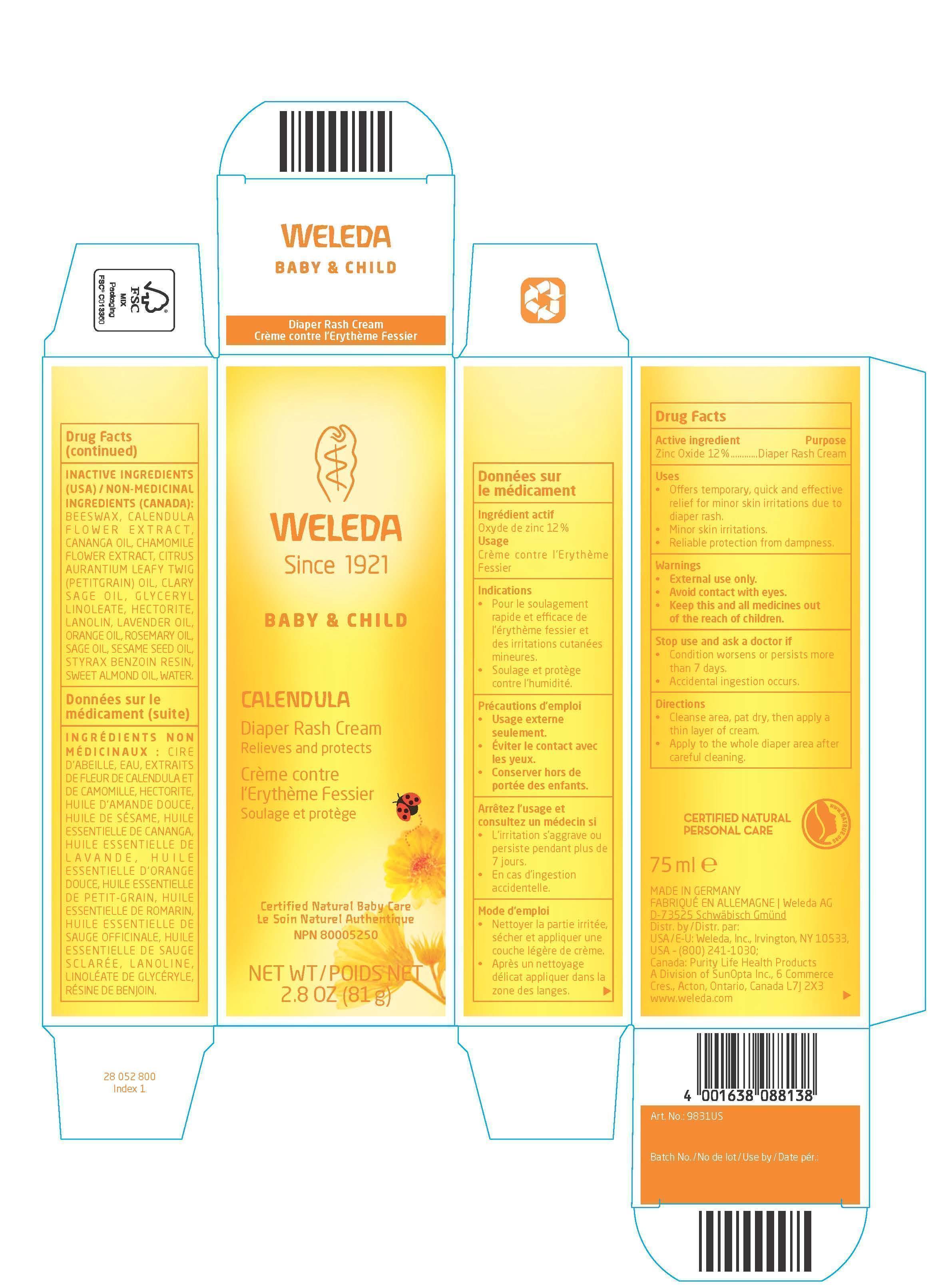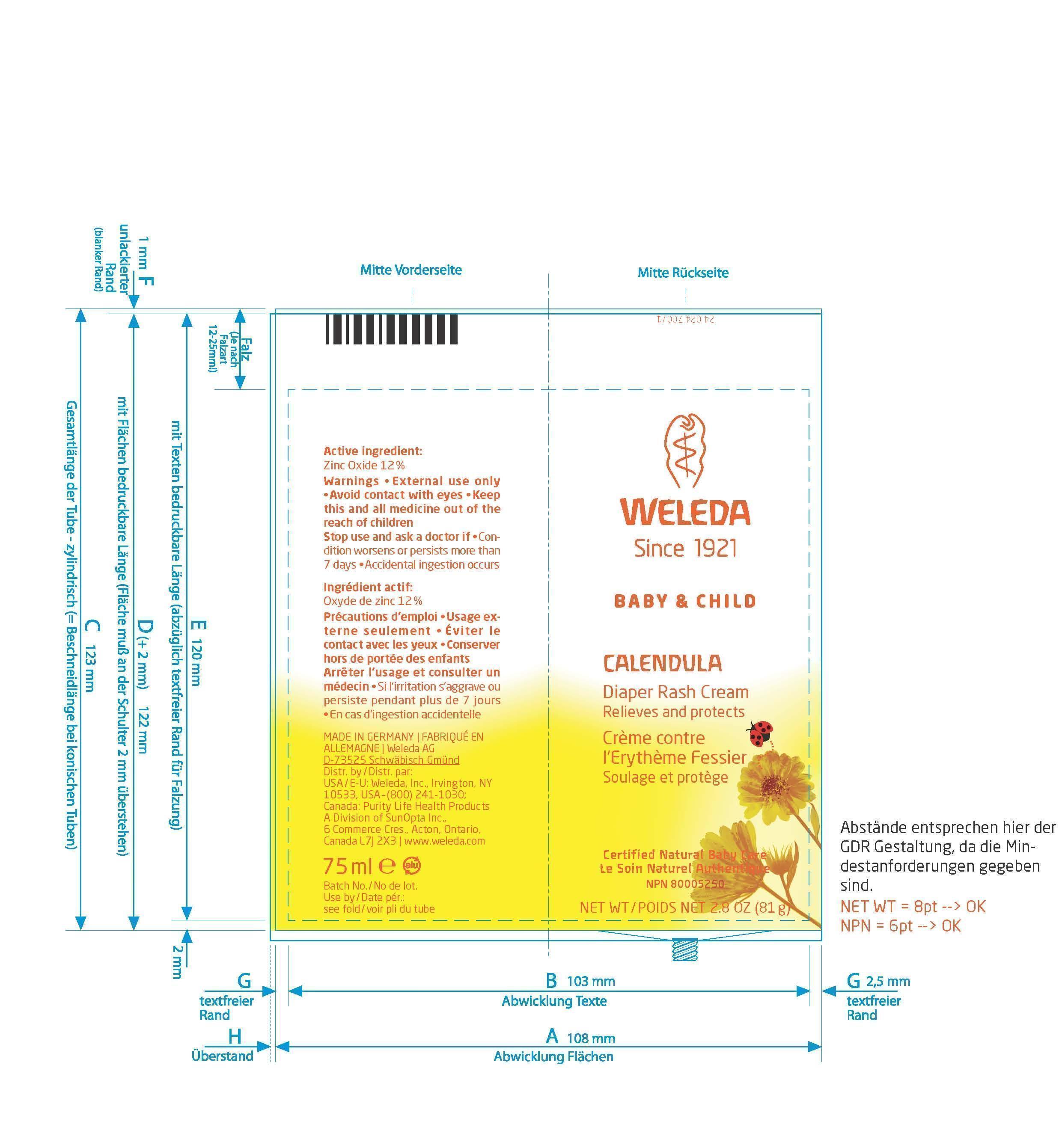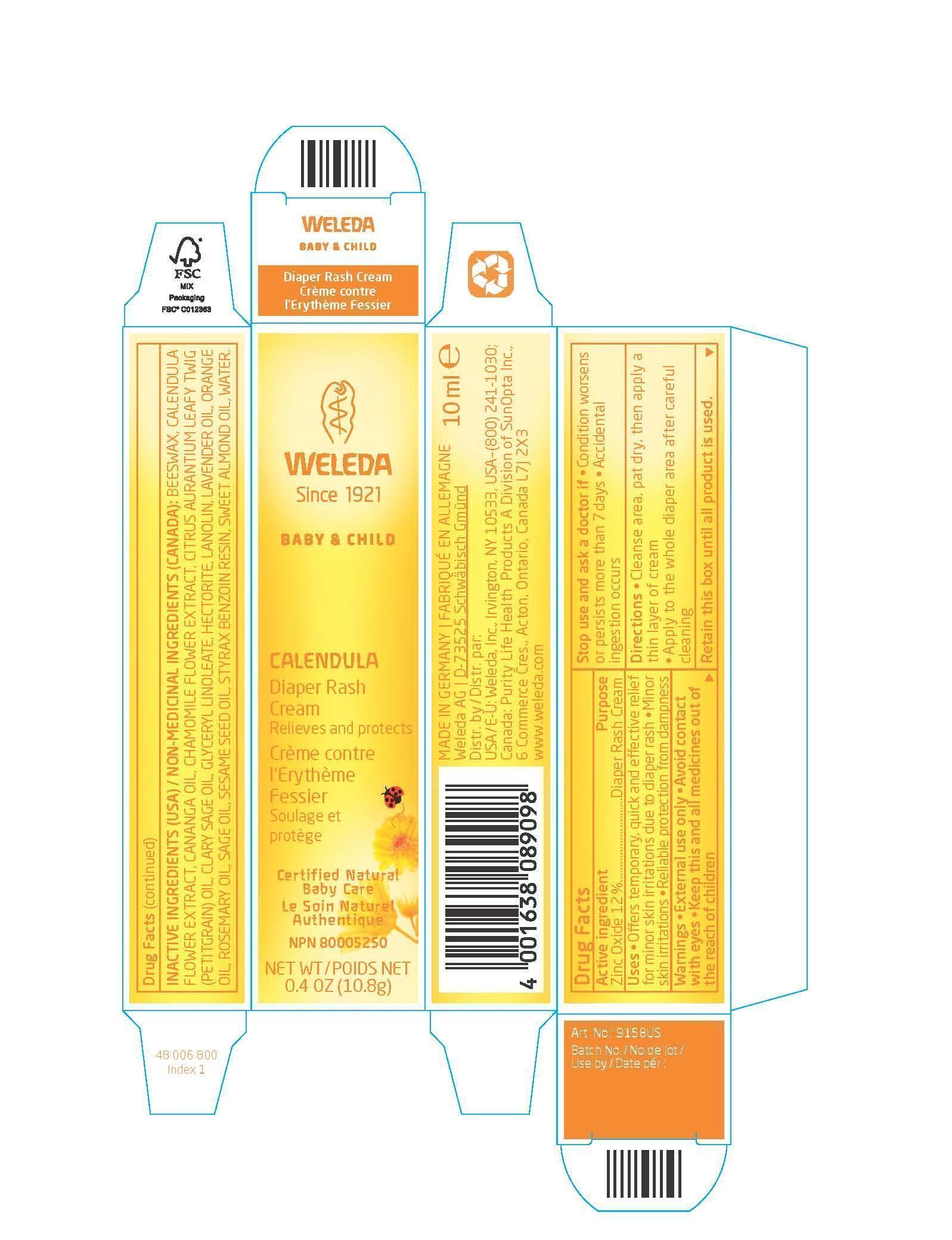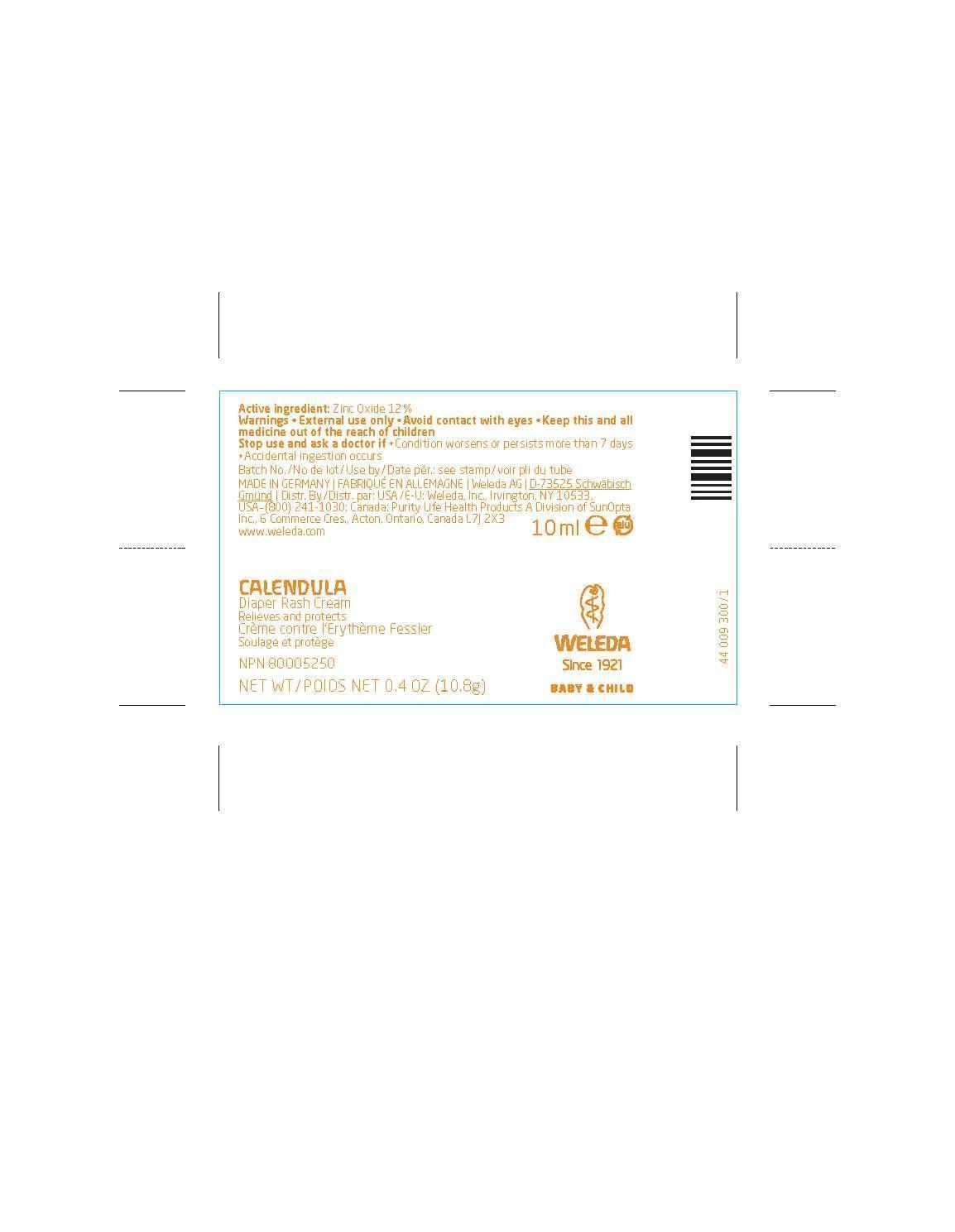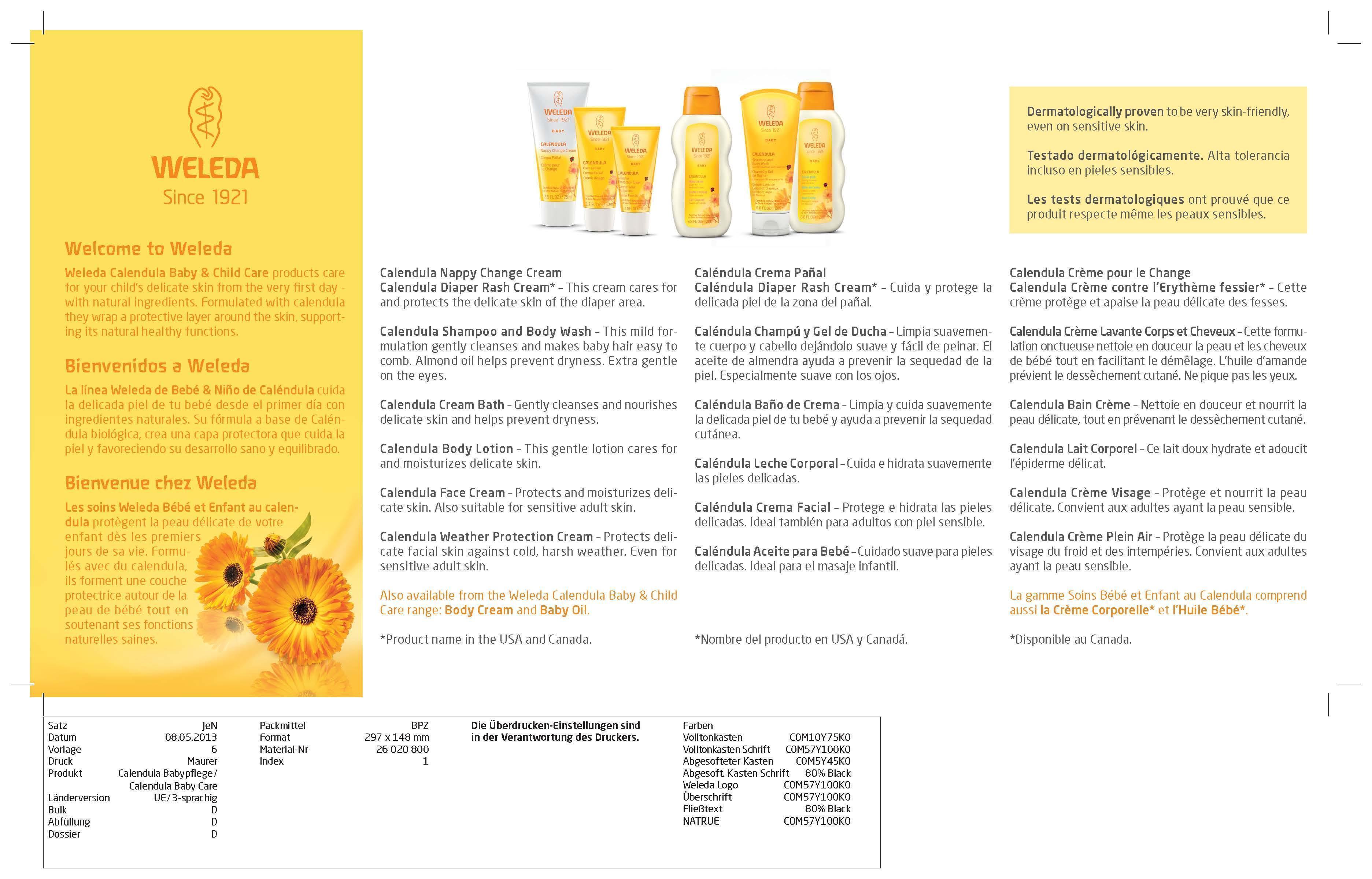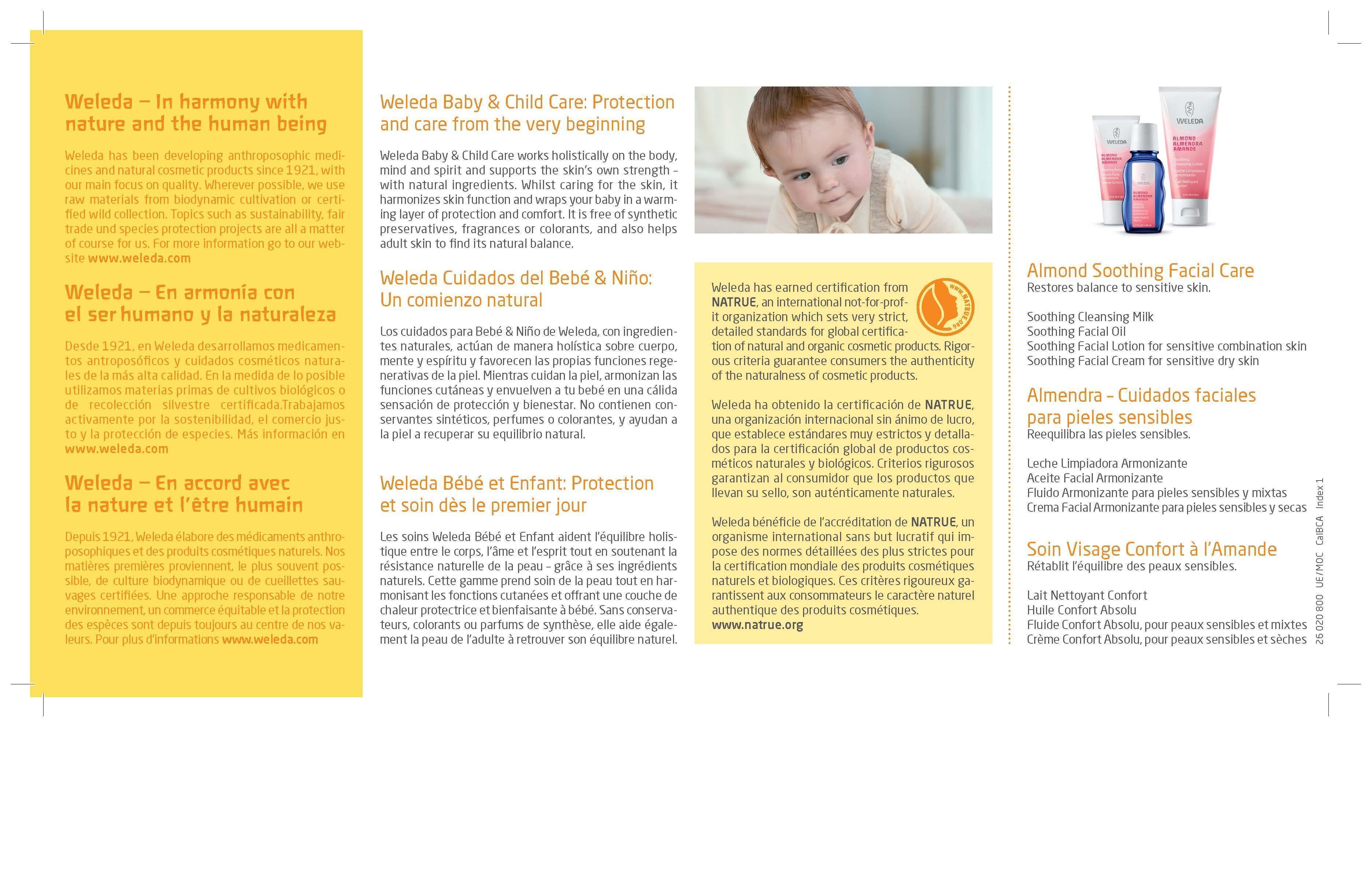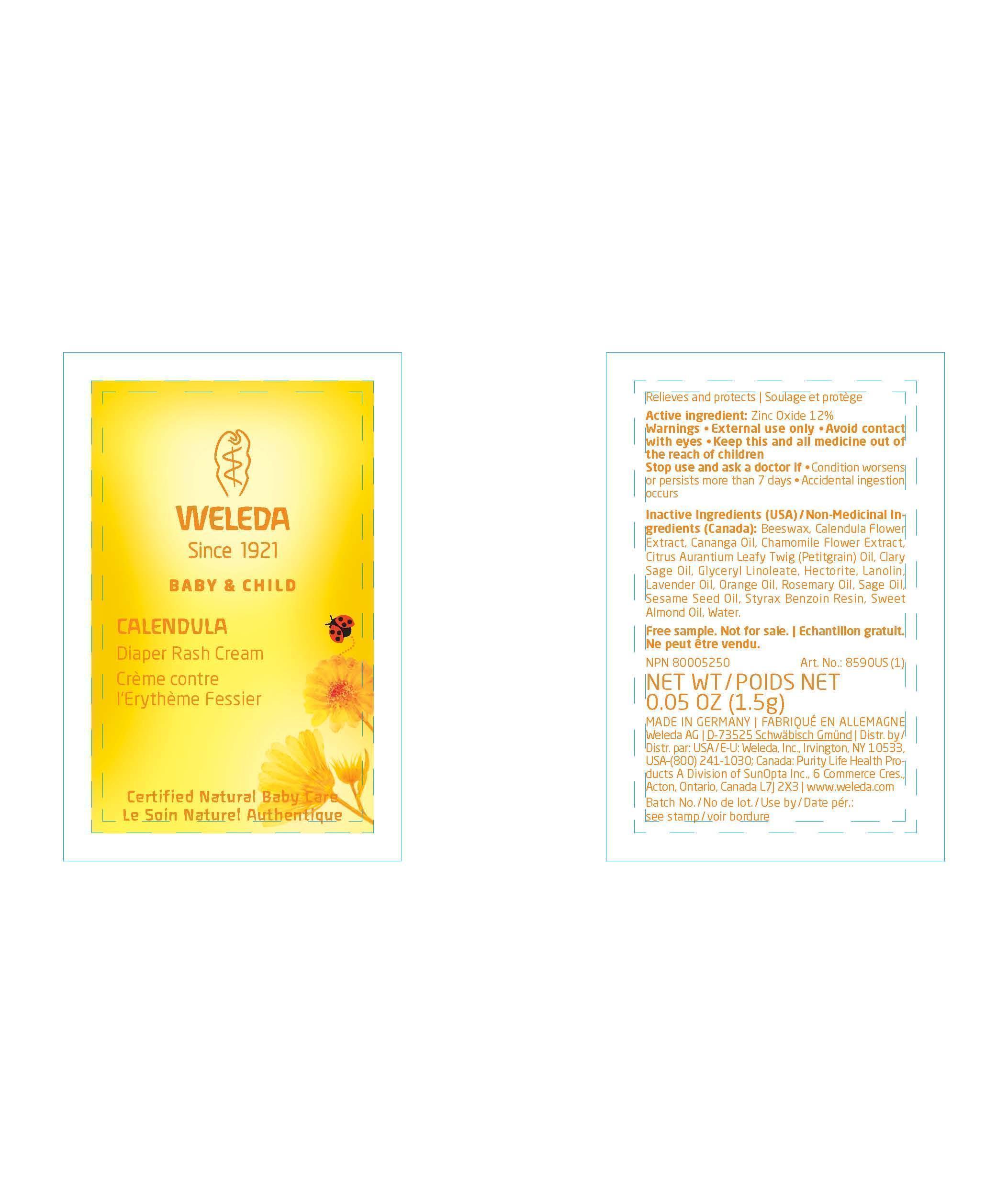 DRUG LABEL: CALENDULA DIAPER RASH CREAM
NDC: 55946-701 | Form: CREAM
Manufacturer: Weleda, Inc.
Category: otc | Type: HUMAN OTC DRUG LABEL
Date: 20130716

ACTIVE INGREDIENTS: ZINC OXIDE 12 g/100 g
INACTIVE INGREDIENTS: YELLOW WAX; CALENDULA OFFICINALIS FLOWER; CANANGA OIL; CHAMOMILE; CITRUS AURANTIUM LEAFY TWIG OIL; CLARY SAGE OIL; GLYCERYL MONOLINOLEATE; HECTORITE; LANOLIN; LAVENDER OIL; ORANGE OIL; ROSEMARY OIL; SAGE OIL; SESAME OIL; STYRAX BENZOIN RESIN; ALMOND OIL; WATER

CALENDULA DIAPER RASH CREAM

PACKAGE LABEL

Weleda

Since 1921

Baby & Child

Calendula

Diaper Rash Cream

Relieves and protects

Crème contre l`Erythème Fessier

Soulage et protège

Certified Natural Baby Care

Le Soin Naturel Authentique

NPN 80005250

NET WT / POIDS NET 2.8 OZ (81g)

Active ingredient

Zinc Oxide 12%

Purpose

Diaper Rash Cream

KEEP OUT OF REACH OF CHILDREN

Keep this and all medicines out of the reach of children.

Uses

Offers temporary, quick and effective relief for minor skin irritations due to diaper rash.

Minor skin irritations.

Reliable protection from dampness.

Warnings

External use only.

Avoid contact with eyes.

Keep this and all medicines out of the reach of children.

Directions

Cleanse area, pat dry, then apply a thin layer of cream.

Apply to the whole diaper area after careful cleaning.

Inactive Ingredients (USA) / Non-Medicinal Ingredients (Canada):

Beeswax, Calendula Flower Extract, Cananga Oil, Chamomile Flower Extract, Citrus Aurantium Leafy Twig (Petitgrain) Oil, Clary Sage Oil, Glyceryl Linoleate, Hectorite, Lanolin, Lavender Oil, Orange Oil, Rosemary Oil, Sage Oil, Sesame Seed Oil, Styrax Benzoin Resin, Sweet Almond Oil, Water.

PACKAGE LABEL

Weleda

Since 1921

Baby & Child

Calendula

Diaper Rash Cream

Relieves and protects

Crème contre l'Erythème Fessier

Soulage et protège

Certified Natural Baby Care

Le Soin Naturel Authentique

NPN 80005250

NET WT / POIDS NET 0.4 OZ (10.8g)

PACKAGE LABEL

Weleda

Since 1921

Baby & Child

Calendula

Diaper Rash Cream

Crème contre l'Erythème Fessier

Certified Natural Baby Care

Le Soin Naturel Authentique

NET WT / POIDS NET 0.05 OZ (1.5g)